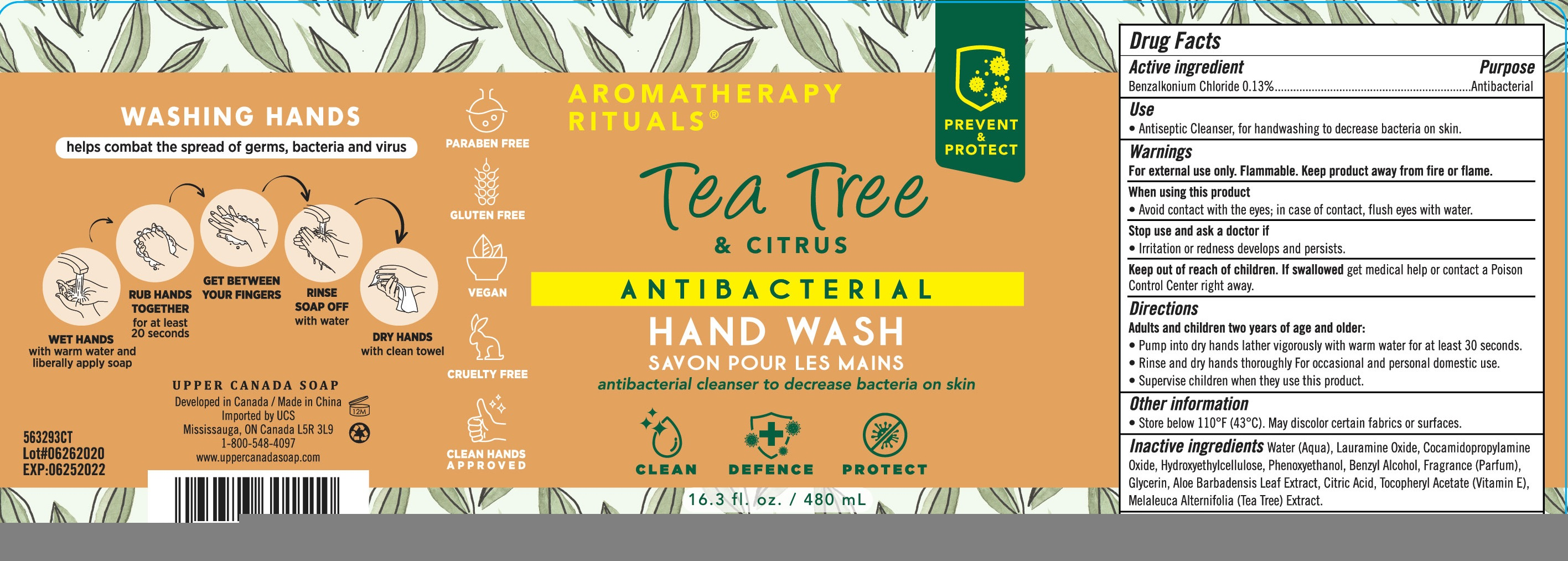 DRUG LABEL: Aromatherapy Rituals Hand Wash Tea Tree and Citrus
NDC: 56136-332 | Form: LIQUID
Manufacturer: Ganzhou Olivee Cosmetic Co., Ltd.
Category: otc | Type: HUMAN OTC DRUG LABEL
Date: 20200624

ACTIVE INGREDIENTS: BENZALKONIUM CHLORIDE 1.3 mg/100 mL
INACTIVE INGREDIENTS: WATER; LAURAMINE OXIDE; COCAMIDOPROPYLAMINE OXIDE; BENZYL ALCOHOL; PHENOXYETHANOL; GLYCERIN; MELALEUCA ALTERNIFOLIA LEAF; ALPHA-TOCOPHEROL

HAND SANITIZER

Active ingredient

BENZALKONIUM CHLORIDE ......0.13%

Purpose

Antibacterial

Use

- Antiseptic cleanser, for handwashing to decrease bacteria on skin.

Warnings

For external use only.

Flammable. Keep product away from fire or flame.

When using this product avoid contact with eyes. In case of contact flush eyes with water.

Stop use and ask a doctor if irritation or redness develops and persists.

Other information:

- Store below 110℉(43℃).
- May discolor certain fabrics or surfaces.

Keep out of reach of children.

If swallowed, get medical help or contact a Poison Control Center right away.

Directions

Adults and children two years of age and older:

- Pump into dry hands lather vigorously with warm water for at lease 30 seconds.
- Rinse and dry hands thoroughly for occasional and personal domestic use.
- Supervise children when they use this product.

Inactive ingredients

Water (Aqua), Lauramine Oxide, Cocamidopropylamine Oxide, Hydroxyethylcellulose, Phenoxyethanol, Benzyl Alcohol, Fragrance (Parfum), Glycerin, Aloe Barbadensis Leaf Extract, Citric Acid, Tocopheryl Acetate (Vitamin E), Melaleuca Alternifolia (Tea Tree) Extract.